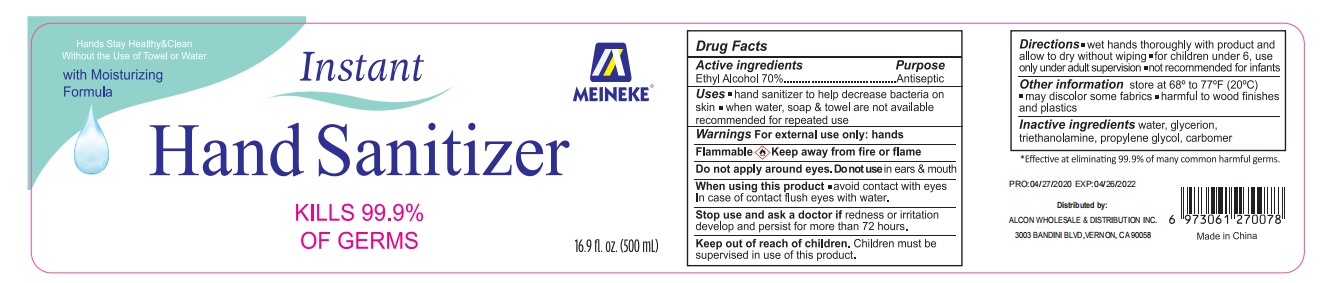 DRUG LABEL: Meineke Instant Hand Sanitizer With Moisturizer Formula
NDC: 75780-011 | Form: LIQUID
Manufacturer: NINGBO MEINEKE Biotech Technology Co., Ltd.
Category: otc | Type: HUMAN OTC DRUG LABEL
Date: 20200709

ACTIVE INGREDIENTS: alcohol 70 mL/100 mL
INACTIVE INGREDIENTS: WATER; PROPYLENE GLYCOL; TROLAMINE; GLYCERIN

hand sanitizer

Active ingredient Purpose

Ethyl Alcohol 70% ... Antiseptic

PURPOSE

Antiseptic

WARNINGS

For external use only.
Flammable. Keep away from fire or flame.

Do not apply around eyes. Do not use in ears and mouth.

When using this products, avoid contact with eyes. In case of contact, flush eyes with water.

Stop using and ask a doctor, if redness and irritation develop and persist for more than 72 hours.

Other information:

- store at 68℉-77℉ (20℃)
- may discolor some fabrics
- harmful to wood finishe and plastics

KEEP OUT OF REACH OF CHILDREN

Children must be supervised in use of this product.

DOSAGE AND ADMINISTRATION

- Wet hands thoroughly with product and allow to dry without wiping
- For children under 6, use only under adult supervision
- Not recommended for infants

INACTIVE INGREDIENT

Water, Triethanolamine, Glycerin, propylene glycol, Carbomer